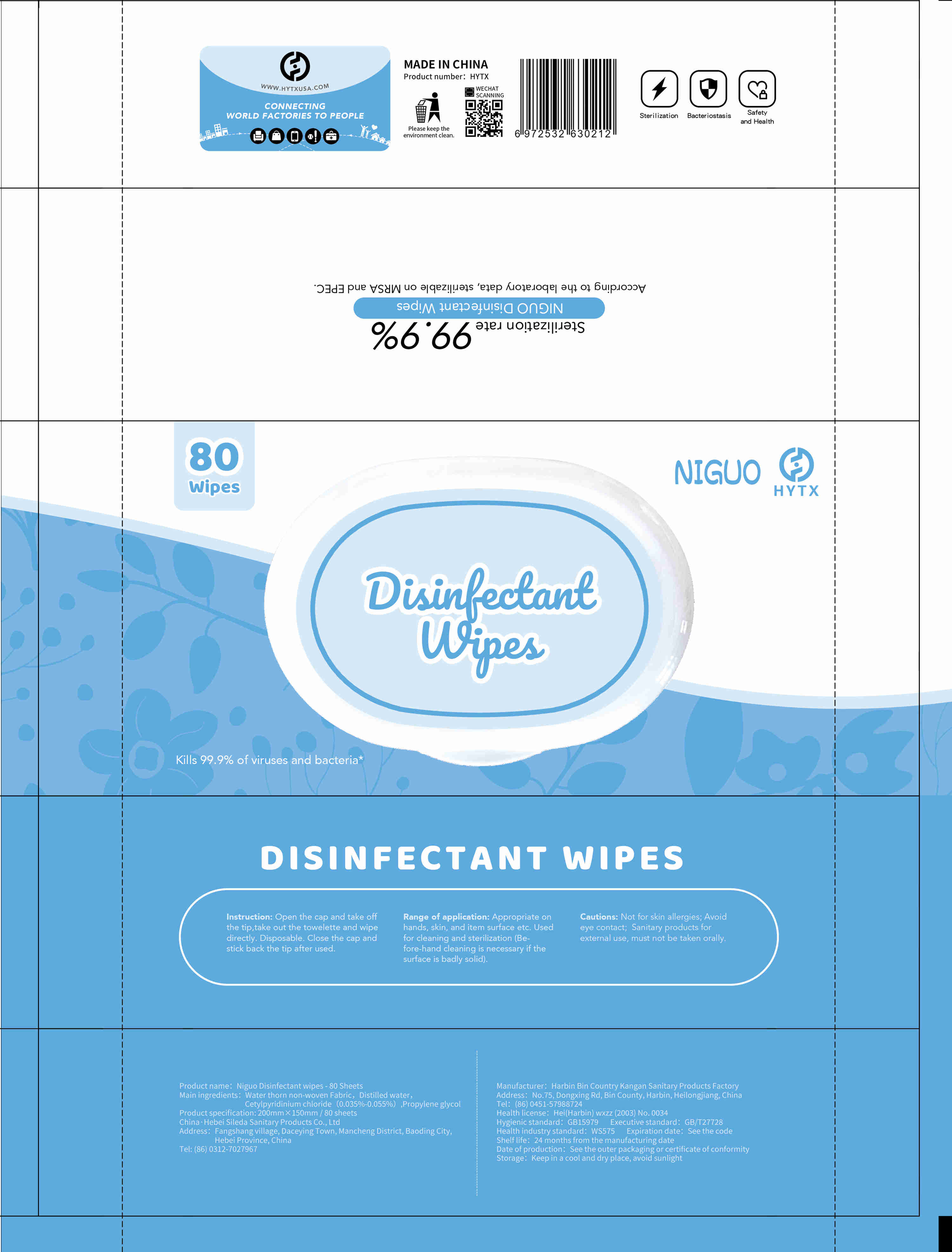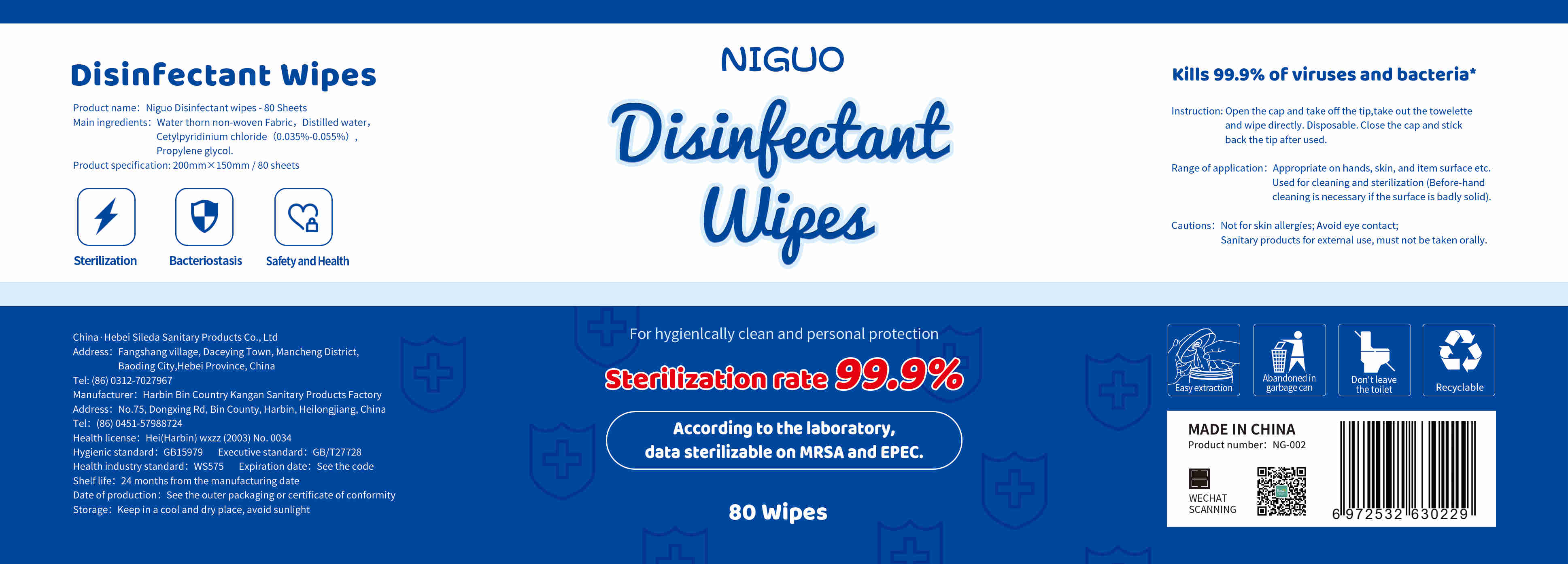 DRUG LABEL: Niguo Disinfectant wipes-80 Sheets
NDC: 92581-002 | Form: CLOTH
Manufacturer: Hebei Sileda Sanitary Products Co., Ltd.
Category: otc | Type: HUMAN OTC DRUG LABEL
Date: 20220406

ACTIVE INGREDIENTS: CETYLPYRIDINIUM CHLORIDE 0.15505 g/80 1; PROPYLENE GLYCOL 2.8352 g/80 1
INACTIVE INGREDIENTS: WATER

DOSAGE AND ADMINISTRATION

Keep in a cool and dry place, avoid sunlight

INACTIVE INGREDIENT

nonwoven spunlace

Water

INDICATIONS AND USAGE

Open the cap and take off the tip,take out the towelette and wipe directly. Disposable. Close the cap and stick back the tip after used.

ACTIVE INGREDIENT

Cetylpyridinium chloride

Propylene glycol

keep out of reach of children

PURPOSE

Disinfection
Sterilization
No Rinseing

WARNINGS

Not for skin allergies; Avoid eye contact;Sanitary products for external use, must not be taken orally.